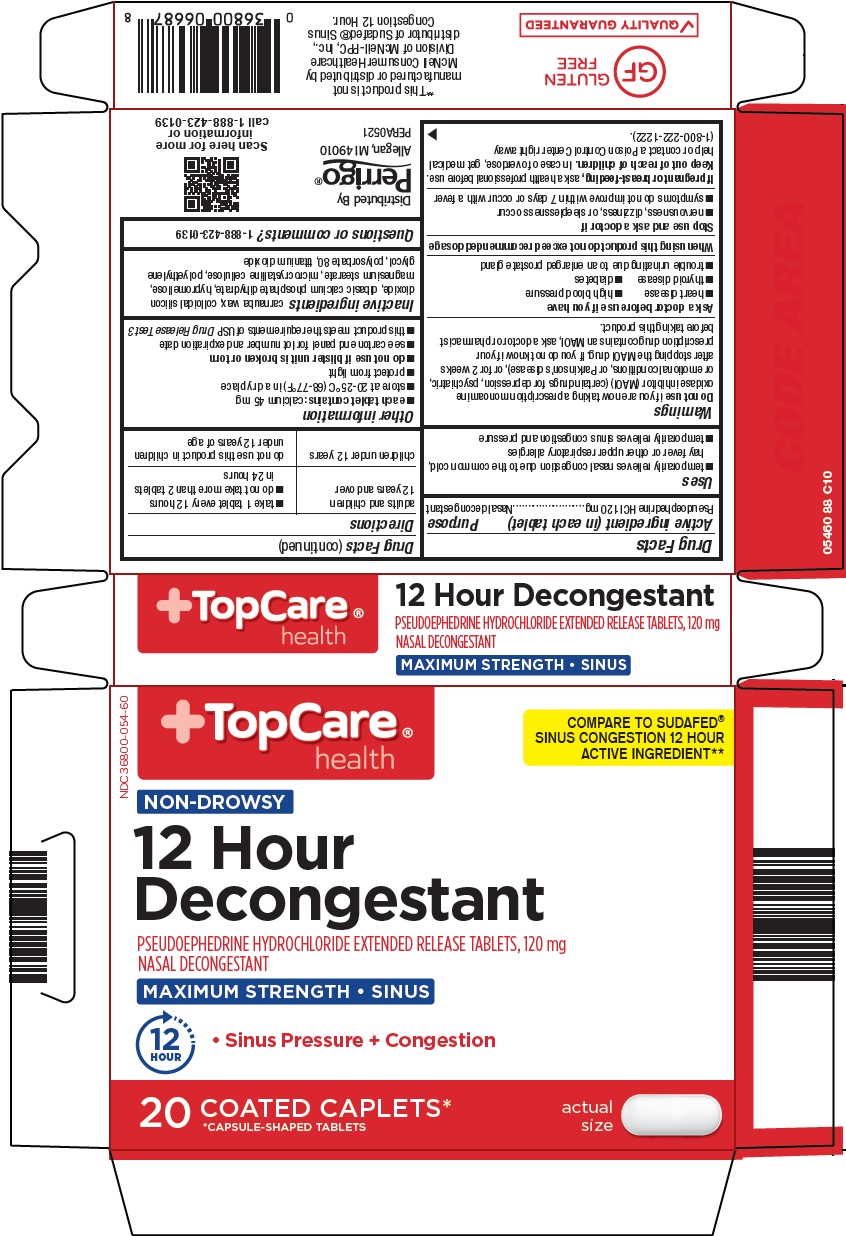 DRUG LABEL: topcare 12 hour decongestant
NDC: 36800-054 | Form: TABLET, FILM COATED, EXTENDED RELEASE
Manufacturer: Topco Associates LLC
Category: otc | Type: HUMAN OTC DRUG LABEL
Date: 20221005

ACTIVE INGREDIENTS: PSEUDOEPHEDRINE HYDROCHLORIDE 120 mg/1 1
INACTIVE INGREDIENTS: CARNAUBA WAX; SILICON DIOXIDE; DIBASIC CALCIUM PHOSPHATE DIHYDRATE; HYPROMELLOSE, UNSPECIFIED; MAGNESIUM STEARATE; MICROCRYSTALLINE CELLULOSE; POLYETHYLENE GLYCOL, UNSPECIFIED; POLYSORBATE 80; TITANIUM DIOXIDE

Topco Associates LLC. 12 Hour Decongestant Drug Facts

Active ingredient (in each tablet)

Pseudoephedrine HCl 120 mg

Purpose

Nasal decongestant

Uses

1. temporarily relieves nasal congestion due to the common cold, hay fever or other upper respiratory allergies
2. temporarily relieves sinus congestion and pressure

Warnings

Do not use

if you are now taking a prescription monoamine oxidase inhibitor (MAOI) (certain drugs for depression, psychiatric, or emotional conditions, or Parkinson’s disease), or for 2 weeks after stopping the MAOI drug. If you do not know if your prescription drug contains an MAOI, ask a doctor or pharmacist before taking this product.

Ask a doctor before use if you have

1. heart disease
2. high blood pressure
3. thyroid disease
4. diabetes
5. trouble urinating due to an enlarged prostate gland

When using this product

do not exceed recommended dosage

Stop use and ask a doctor if

1. nervousness, dizziness, or sleeplessness occur
2. symptoms do not improve within 7 days or occur with a fever

If pregnant or breast-feeding,

ask a health professional before use.

Keep out of reach of children.

In case of overdose, get medical help or contact a Poison Control Center right away (1-800-222-1222).

Directions

adults and children 12 years and over | 1. take 1 tablet every 12 hours 2. do not take more than 2 tablets in 24 hours
children under 12 years | do not use this product in children under 12 years of age

Other information

- each tablet contains: calcium 45 mg
- store at 20-25°C (68-77°F) in a dry place
- protect from light
- do not use if blister unit is broken or torn
- see carton end panel for lot number and expiration date
- this product meets the requirements of USP Drug Release Test 3

Inactive ingredients

carnauba wax, colloidal silicon dioxide, dibasic calcium phosphate dihydrate, hypromellose, magnesium stearate, microcrystalline cellulose, polyethylene glycol, polysorbate 80, titanium dioxide

Questions or comments?

1-888-423-0139

Principal Display Panel

TopCare® health

COMPARE TO SUDAFED® SINUS CONGESTION 12 HOUR ACTIVE INGREDIENT

NON-DROWSY

12 Hour Decongestant

PSEUDOEPHEDRINE HYDROCHLORIDE EXTENDED RELEASE TABLETS, 120 mg

NASAL DECONGESTANT

MAXIMUM STRENGTH • SINUS

12 HOUR

• Sinus Pressure + Congestion

20 COATED CAPLETS*

*CAPSULE-SHAPED TABLETS

actual size